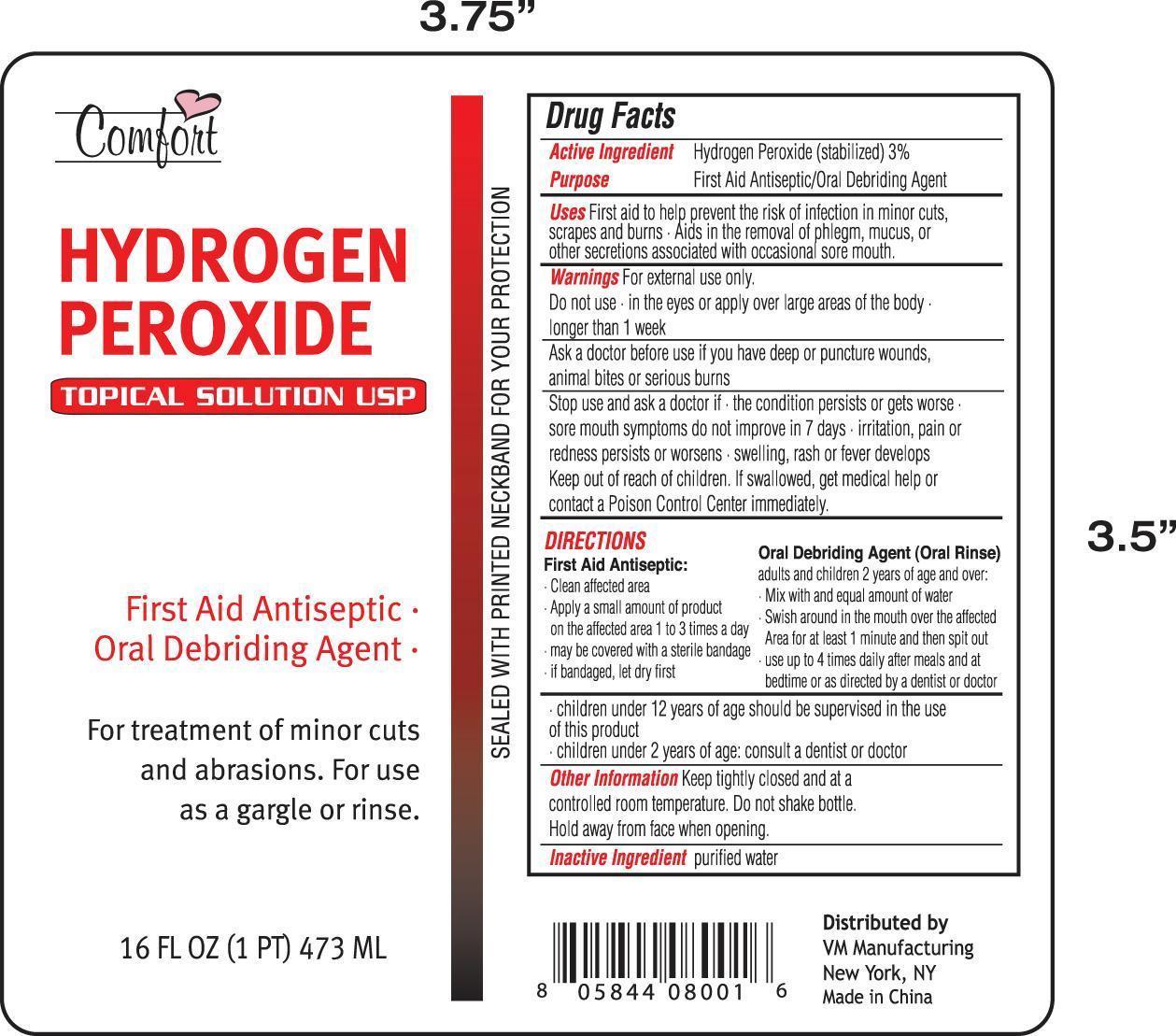 DRUG LABEL: COMFORT
NDC: 50827-650 | Form: LIQUID
Manufacturer: Weimei Lianyungang Household Articles manufacturing, Co. LTD
Category: otc | Type: HUMAN OTC DRUG LABEL
Date: 20120524

ACTIVE INGREDIENTS: HYDROGEN PEROXIDE 2.65 mL/100 mL
INACTIVE INGREDIENTS: WATER

Active Ingredient

Hydrogen Peroxide (Stablized) 3%

Package Label

Hydrogen Peroxide

Purpose

First Aid Antiseptics/Oral Debriding Agent

Uses

First aid to help prevent the risk of infection in minor cuts, scrapes and burns. Aids in the removal of phlegm, mucus, or other secrections assocated with occasional sore mouth

Warnings

For External Use only

Do not use: in the eyes or apply over large areas of the body longer than a week

Ask a doctor bbefore use if you have deep or punture wounds, animal bits or serious burns

Stop use and ask a doctor if the condition persists or gets worse. Sore mouth symptoms do not improve in 7 days.

Irriation, pain or redness persists or worsens. swelling, rash, or fever develops. Keep reach out of children. If swallowed, get medical help or contact a poison control center immediately.

KEEP OUT OF REACH OF CHILDREN

Keep reach out of children. If swallowed, get medical help or contact a poison control center immediately.

Directions

first aid antiseptic:

clean affected area
apply small amount of product on affected area 1-3 times a day
may be covered with a sterile bandage
if bandage, let dry first

oral debriding agent (oral rinse):

adults and children 2 years of age and over
mix with an equal amount of water
swish around in the mouth over affected area for atleast 1 minute and spit out
use up to 4x daily after meals and at bedtime or as directed by a dentist or doctor.

children under 12 years should be supervised in the use of this product
children under 2 years of age; consult a dentist or doctor

DOSAGE AND ADMINISTRATION

first aid antiseptic:

clean affected area
apply small amount of product on affected area 1-3 times a day
may be covered with a sterile bandage
if bandage, let dry first

oral debriding agent (oral rinse):

adults and children 2 years of age and over
mix with an equal amount of water
swish around in the mouth over affected area for atleast 1 minute and spit out
use up to 4x daily after meals and at bedtime or as directed by a dentist or doctor.

children under 12 years should be supervised in the use of this product
children under 2 years of age; consult a dentist or doctor

Other Information

Keep tightly closed and in a dark place at a controlled room temperature. Do not shake bottle. Hold away from face when opening.

Inactive Ingredient

Purified water